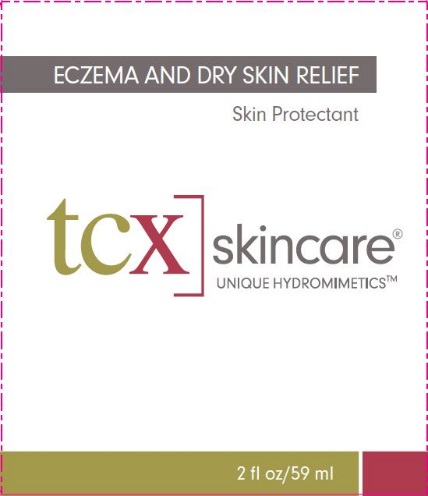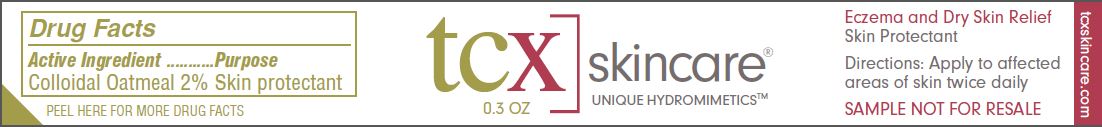 DRUG LABEL: TCX Skincare
NDC: 49449-100 | Form: CREAM
Manufacturer: Theraceutix, LLC
Category: otc | Type: HUMAN OTC DRUG LABEL
Date: 20251224

ACTIVE INGREDIENTS: OATMEAL 2 g/100 g
INACTIVE INGREDIENTS: WATER; GLYCERIN; CARBOMER COPOLYMER TYPE A (ALLYL PENTAERYTHRITOL CROSSLINKED); CETYL PALMITATE; MINERAL OIL; MEDIUM-CHAIN TRIGLYCERIDES; CETYL ALCOHOL; GLYCERYL 1-STEARATE; DIMETHICONE, UNSPECIFIED; PEG-40 MONOSTEARATE; SODIUM HYDROXIDE; PHENOXYETHANOL; DMDM HYDANTOIN; IODOPROPYNYL BUTYLCARBAMATE; OCTYLDODECANOL

tcx skincare® Unique Hydromimetics™

Active Ingredient

Colloidal Oatmeal 2%

Purpose

Skin protectant

Uses

- Temporarily protects and helps relieve minor skin irritation and itching due to dry skin and eczema

Warnings

- For external use only

Keep out of reach of children.

If swallowed, get medical help or contact a Poison Control Center right away.

When using this product:

- Do not get into eyes
- Stop use and ask doctor if condition worsens

Directions

- Apply to affected areas of skin twice daily

Inactive Ingredients

Caprylic/Capric Triglyceride, Carbomer, Cetyl Alcohol, Cetyl Palmitate, Dimethicone, DMDM Hydantoin, Glycerin, Glyceryl Stearate, Iodopropynyl Butylcarbamate, Mineral Oil, Octyldodecanol, PEG-40 Stearate, Phenoxy Ethanol, Sodium Hydroxide, Water

Package/Label Principal Display Panel - Carton Label

ECZEMA AND DRY SKIN RELIEF
Skin Protectant

tcx skincare®
UNIQUE HYDROMIMETICS™

2 fl oz/59 mL

Carton Label

Package/Label Principal Display Panel - Sample Label

tcx skincare®
UNIQUE HYDROMIMETICS™

0.3 oz

Eczema and Dry Skin Relief
Skin Protectant

Directions: Apply to affected areas of skin twice daily

SAMPLE NOT FOR RESALE

tcxskincare.com

Sample Label